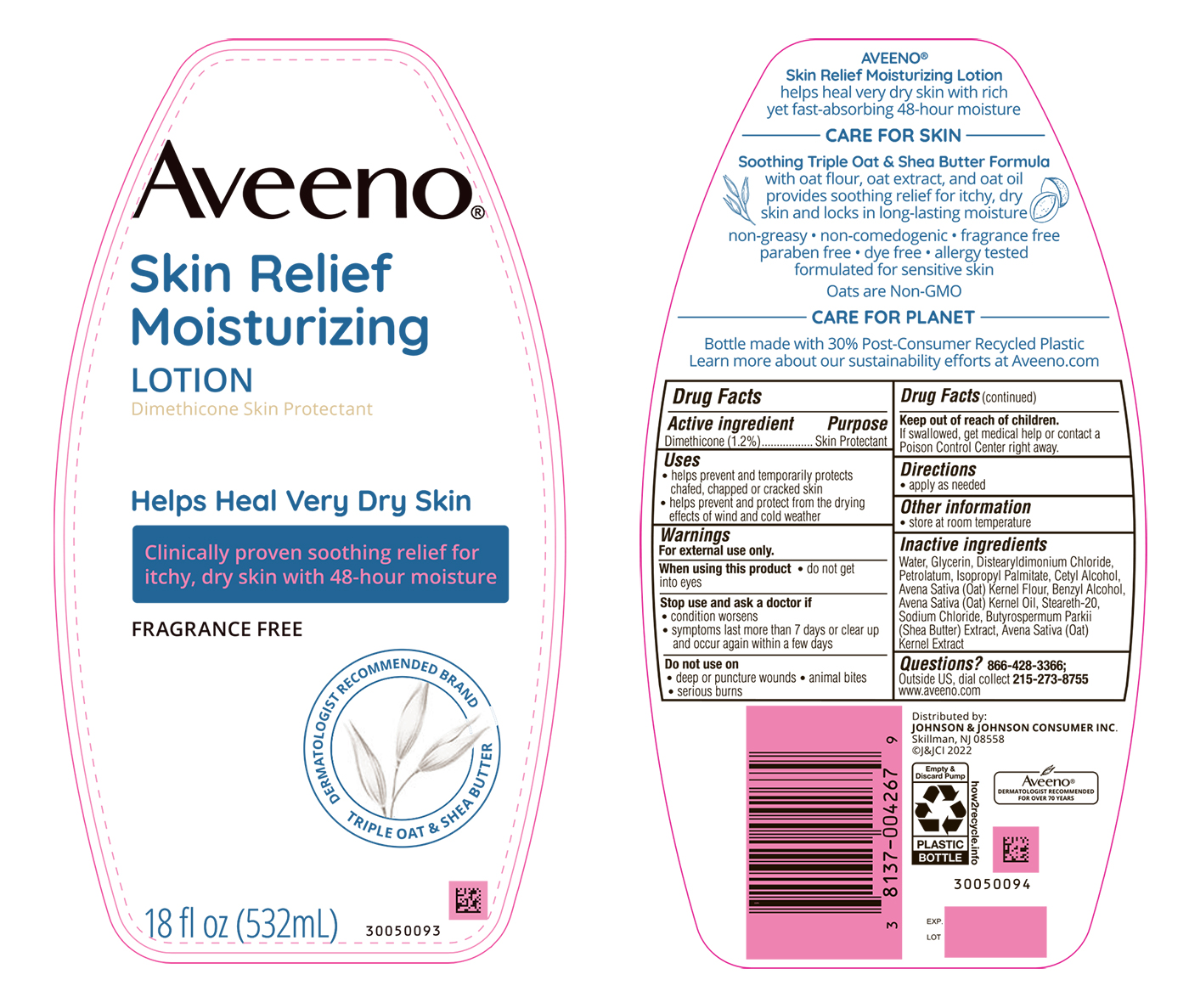 DRUG LABEL: Aveeno Skin Relief Moisturizing
NDC: 69968-0408 | Form: LOTION
Manufacturer: Kenvue Brands LLC
Category: otc | Type: HUMAN OTC DRUG LABEL
Date: 20241105

ACTIVE INGREDIENTS: DIMETHICONE 12 mg/1 mL
INACTIVE INGREDIENTS: GLYCERIN; WATER; DISTEARYLDIMONIUM CHLORIDE; PETROLATUM; ISOPROPYL PALMITATE; CETYL ALCOHOL; OATMEAL; BENZYL ALCOHOL; OAT KERNEL OIL; STEARETH-20; SODIUM CHLORIDE; SHEANUT; OAT

Aveeno® SKIN RELIEF MOISTURIZING Lotion Fragrance Free

Drug Facts

Active Ingredient

Dimethicone 1.2%

Purpose

Skin Protectant

Uses

- helps prevent and temporarily protects chafed, chapped, or cracked skin
- helps prevent and protect from the drying effects of wind and cold weather

Warnings

For external use only.

When using this product

- do not get into eyes.

Stop use and ask a doctor if

- condition worsens
- symptoms last more than 7 days or clear up and occur again within a few days.

Do not use on

- deep or puncture wounds
- animal bites
- serious burns

Keep out of reach of children. If swallowed, get medical help or contact a Poison Control Center right away.

Directions

- apply as needed.

Other Information

- store at room temperature

Inactive Ingredients

Water, Glycerin, Distearyldimonium Chloride, Petrolatum, Isopropyl Palmitate, Cetyl Alcohol, Avena Sativa (Oat) Kernel Flour, Benzyl Alcohol, Avena Sativa (Oat) Kernel Oil, Steareth-20, Sodium Chloride, Butyrospermum Parkii (Shea Butter) Extract, Avena Sativa (Oat) Kernel Extract

Questions?

866-428-3366; Outside US, dial collect 215-273-8755 www.aveeno.com

Distributed by:
JOHNSON & JOHNSON
CONSUMER INC.
Skillman, NJ 08558

PRINCIPAL DISPLAY PANEL - 532 mL Bottle Label

Aveeno®

Skin Relief

Moisturizing

LOTION

Dimethicone skin protectant

Helps Heal Very Dry Skin

Clinically proven soothing relief for

itchy, dry skin with 48-hour moisture

FRAGRANCE FREE

DERMATOLOGIST RECOMMENDED BRAND

TRIPLE OAT & SHEA BUTTER

18 fl oz (532 mL)